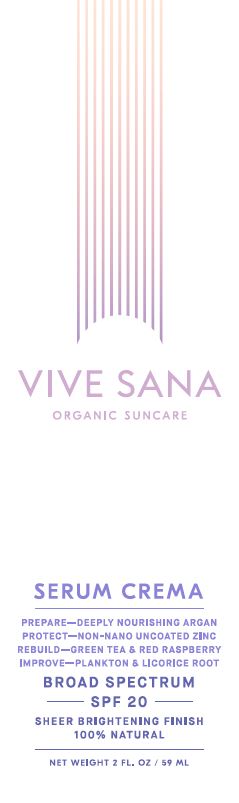 DRUG LABEL: Serum Crema
NDC: 71556-200 | Form: LOTION
Manufacturer: Pure on Purpose, LLC
Category: otc | Type: HUMAN OTC DRUG LABEL
Date: 20190118

ACTIVE INGREDIENTS: ZINC OXIDE 13.5 g/100 g
INACTIVE INGREDIENTS: ARGAN OIL; CAMELLIA SINENSIS SEED OIL; SAFFLOWER OIL; GLYCERIN; GLYCYRRHIZA GLABRA; HAEMATOCOCCUS PLUVIALIS; SUNFLOWER OIL; AVOCADO OIL; APRICOT KERNEL OIL; ROSEMARY; RASPBERRY SEED OIL; JOJOBA OIL; TOCOPHEROL

Serum Crema Broad Spectrum SPF20 Sunscreen

Active Ingredient

Zinc Oxide (non-nano uncoated) 13.5%

Purpose

Sunscreen

USES

Helps prevent sunburn. If used as directed with other sun protection measures (see Directions), decreases the risk of skin cancer and early skin aging caused by the sun.

WARNINGS

Do not use on damaged or broken skin. When using this product keep out of eyes. Rinse with water to remove. Stop use and ask a doctor if rash occurs.

DIRECTIONS

- Apply liberally 15 minutes before sun exposure
- Children under 6 months of age—ask a doctor
- Sun Protection Measures. Spending time in the sun increases your risk of skin cancer and early skin aging. To decrease this risk, regularly use a sunscreen with a Broad Spectrum SPF value of 15 or higher & other sun protection measures including:
  - limit time in the sun, especially from 10am–2pm
  - wear long-sleeved shirts, pants, hats & sunglasses
  - use a water-resistant sunscreen if swimming or sweating
  - reapply at least every 2 hours

OTHER INFORMATION

Protect this product from excessive heat & direct sunlight.

INACTIVE INGREDIENTS

Argania Spinosa Kernel Oil* (Argan), Camellia Sinensis (Green Tea) Seed Oil*, Carthamus Tinctorius (Safflower) Seed Oil*, Cera Alba (Beeswax)*, Glycerin*, Glycyrrhiza Glabra (Licorice) Root Extract, Haematococcus Pluvialis Extract (Astaxanthin derived from Plankton), Helianthus Annuus (Sunflower) Seed Oil*, Iron Oxides (CI 77491) & (CI 77492), Jojoba Esters, Persea Gratissima (Avocado) Oil*, Prunus Armeniaca (Apricot) Kernel Oil*, Rosmarinus Officinalis (Rosemary) Leaf Extract, Rubus Idaeus (Raspberry) Seed Oil, Simmondsia Chinensis (Jojoba) Seed Oil*, Tocopherol (Vitamin E). *denotes certified organic

Package/Label Principal Display Panel

VIVE SANA
ORGANIC SUNCARE

SERUM CREMA
PREPARE-DEEPLY NOURISHING ARGAN
PROTECT-NON-NANO UNCOATED ZINC
REBUILD-GREEN TEA & RED RASPBERRY
IMPROVE-PLANKTON & LICORICE ROOT
BROAD SPECTRUM
-SPF 20-
SHEER BRIGHTENING FINISH
100% NATURAL

NET WEIGHT 2 FL. OZ / 59 ML

Label